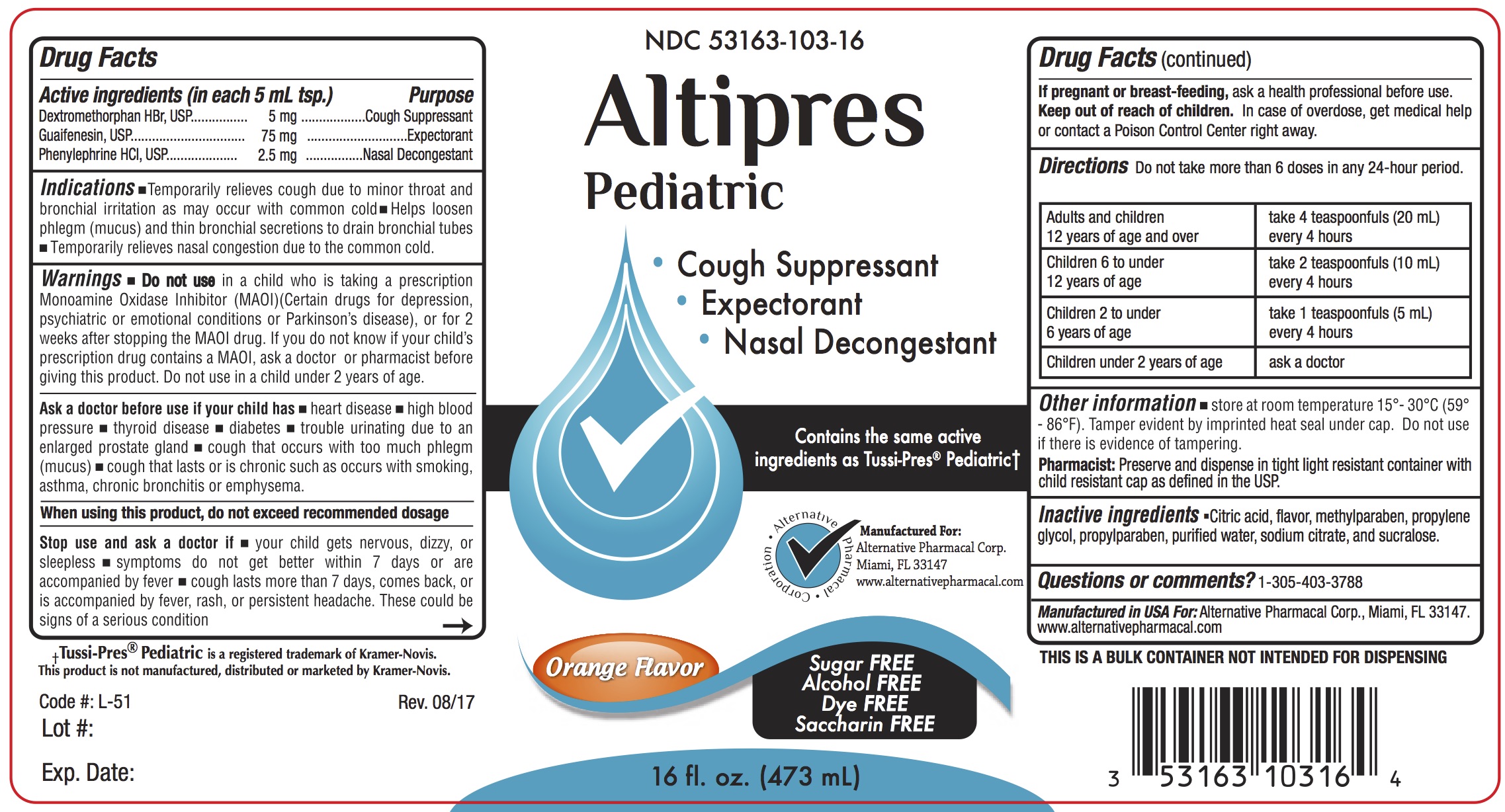 DRUG LABEL: Altipres
NDC: 53163-103 | Form: LIQUID
Manufacturer: Alternative Pharmacal Corporation
Category: otc | Type: HUMAN OTC DRUG LABEL
Date: 20241223

ACTIVE INGREDIENTS: DEXTROMETHORPHAN HYDROBROMIDE 5 mg/5 mL; GUAIFENESIN 75 mg/5 mL; PHENYLEPHRINE HYDROCHLORIDE 2.5 mg/5 mL
INACTIVE INGREDIENTS: SUCRALOSE; CITRIC ACID MONOHYDRATE; METHYLPARABEN; PROPYLENE GLYCOL; PROPYLPARABEN; WATER; SODIUM CITRATE

Alt-AltipresPed 103

Active Ingredients (in each 5 mL tsp.) Purpose

Dextromethorphan HBr ............... 5 mg ................ Cough Suppressant

Guaifenesin .............................. 75 mg ................ Expectorant

Phenylephrine HCl ..................... 2.5 mg ................... Nasal Decongestant

Purpose

Cough Suppressant

Expectorant

Nasal Decongestant

Warnings

Ask a doctor before use if your child has

- heart disease
- high blood pressure
- thyroid disease
- diabetes
- trouble urinating due to the enlargement of the prostate gland
- a cough that occurs with too much phlegm (mucus)
- cough that lasts or is chronic as occurs with smoking, asthma, chronic bronchitis or emphysema

When using this product, do not exceed recommended dosage
Stop use and ask doctor if

- your child gets nervous, dizzy or sleepless
- symptoms do not get better within 7 days or are accompanied by fever
- cough lasts more than 7 days, comes back or is accompanied by fever, rash or persistent headache. These could be signs of a serious condition

DO NOT USE

Do not usein a child who is taking a prescription Monoamine Oxidase Inhibitor (MAOI) (certain drugs for depression, psychiatric or emotional conditions or Parkinson's disease), or for 2 weeks after stopping the MAOI drug. If you do not know if your child's prescription drug contains an MAOI; ask a doctor or pharmacist before taking this product -Do not use- in a child under 2 years of age.

PREGNANCY OR BREAST FEEDING

If pregnant or breast-feeding,ask a health professional before use.

Keep out of reach of children.In case of overdose, get medical help or contact a Poison Control Center right away.

Indications

- Temporarily relieves cough due to minor throat and bronchial irritation as may occur with common cold
- helps loosen phlegm (mucus) and thin bronchial secretions to drain bronchial tubes
- temporarily relieves nasal congestion due to the common cold

DOSAGE AND ADMINISTRATION

Directions Do not exceed more than 6 doses in any 24-hour period

adults and children 12 years of age and over | take 4 teaspoonfuls (20 mL) every 4 hours
children 6 to under 12 years of age | take 2 teaspoonful (10 mL) every 4 hours
children 2 years to under 6 years of age | take 1 teaspoonful (5 mL) every 4 hours
children under 2 years of age | ask a doctor

INACTIVE INGREDIENT

Inactive ingredients citric acid, flavor, methylparaben, propylene glycol, propylparaben, purified water, sodium citrate and sucralose

Questions or comments?1-305-403-3788